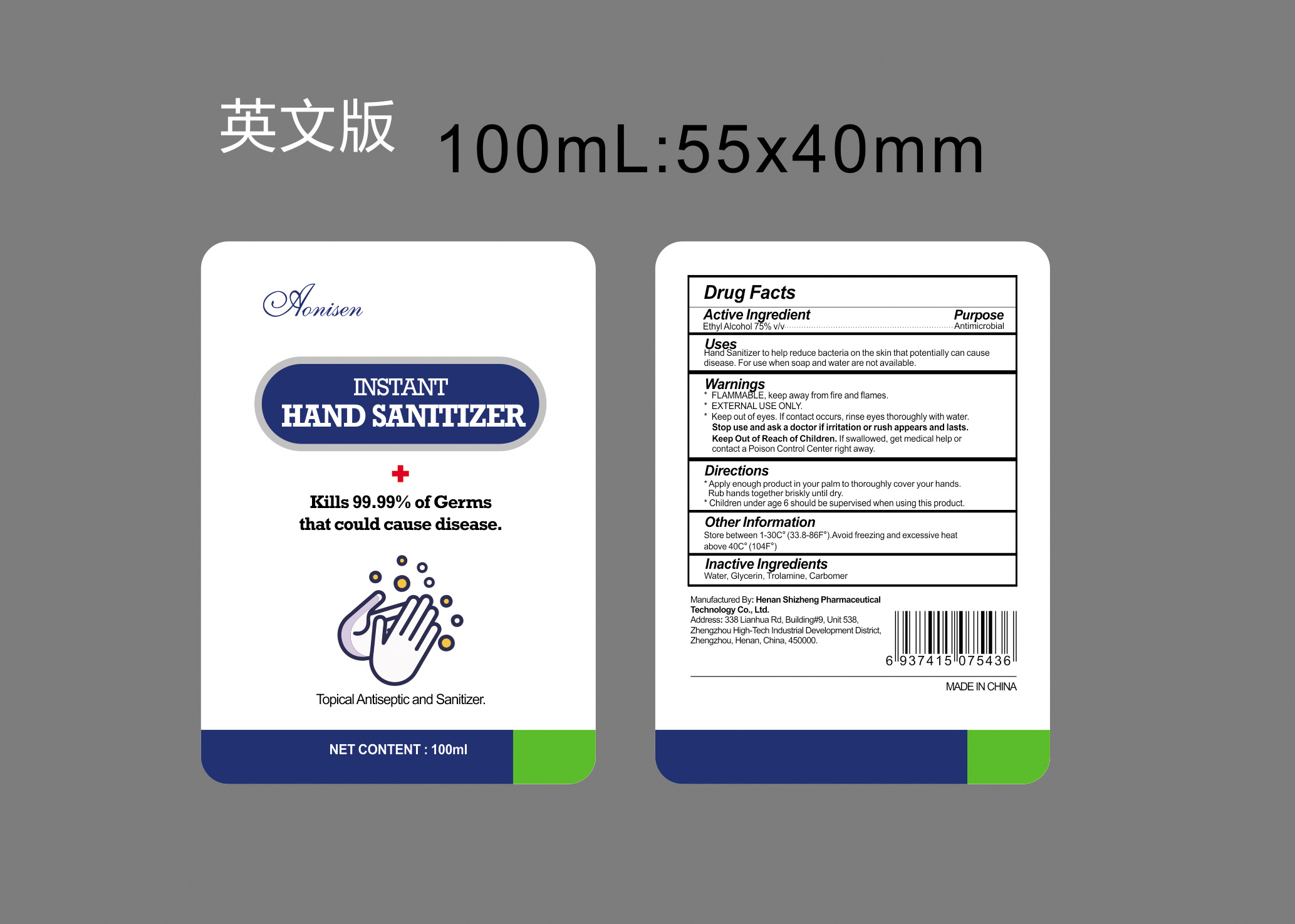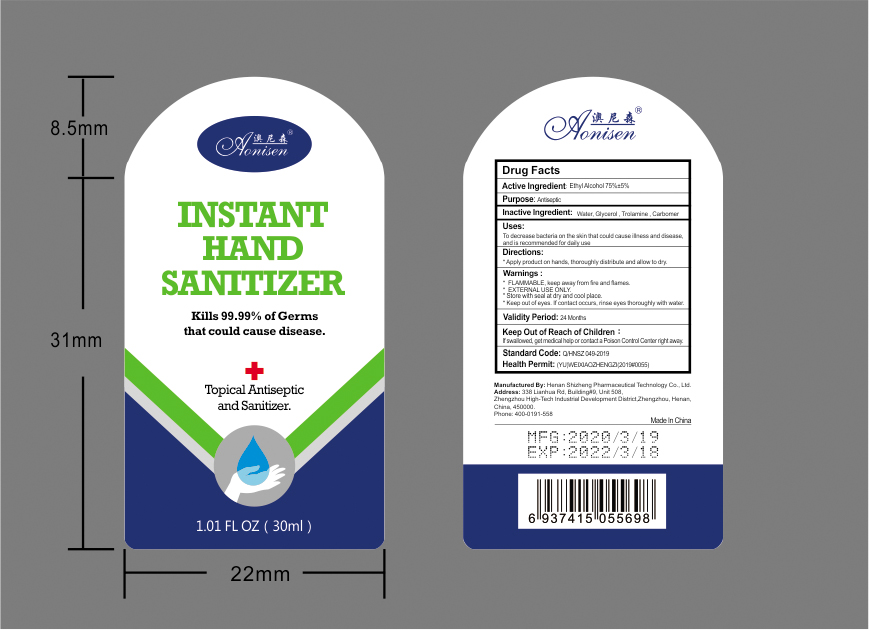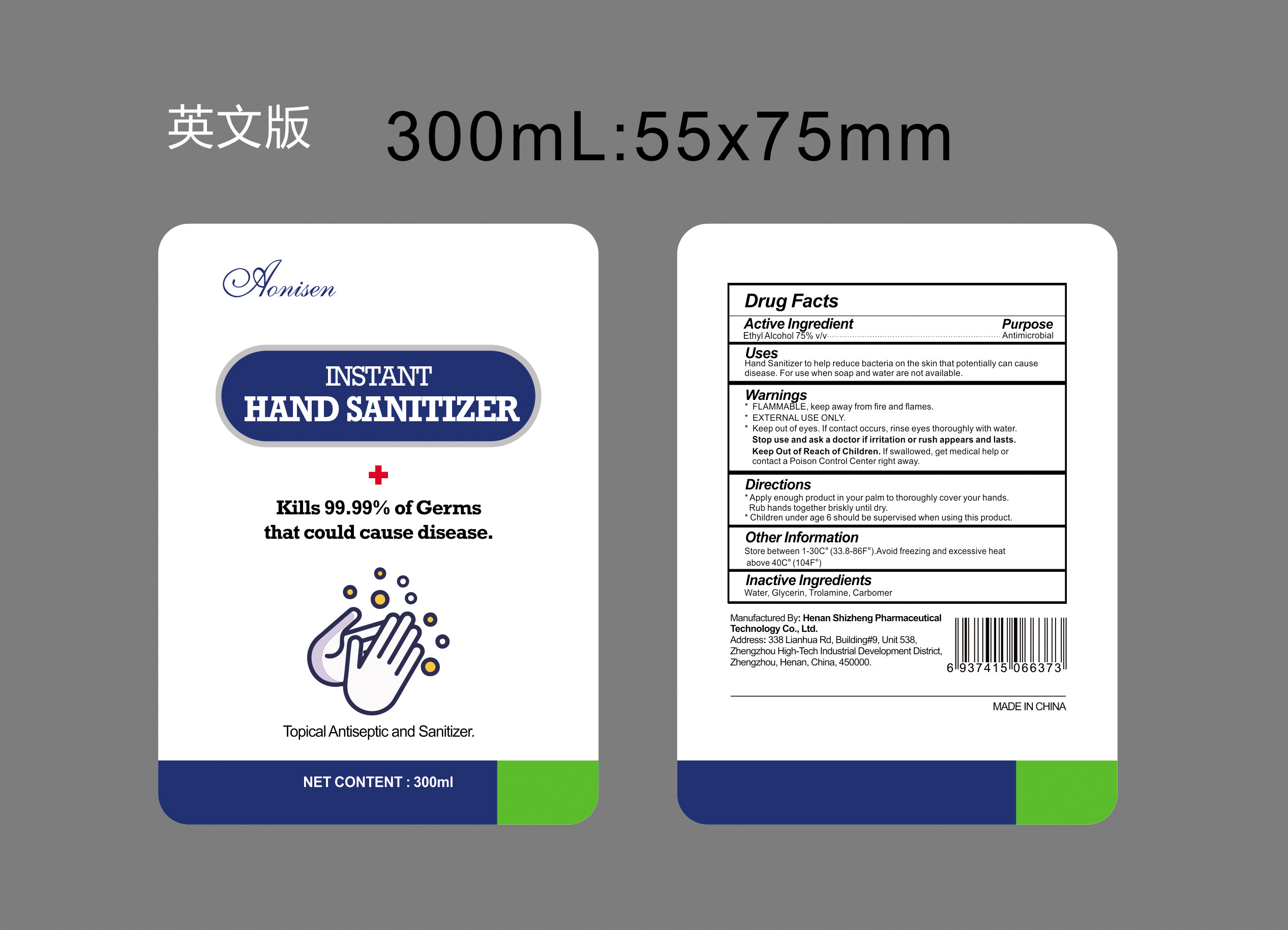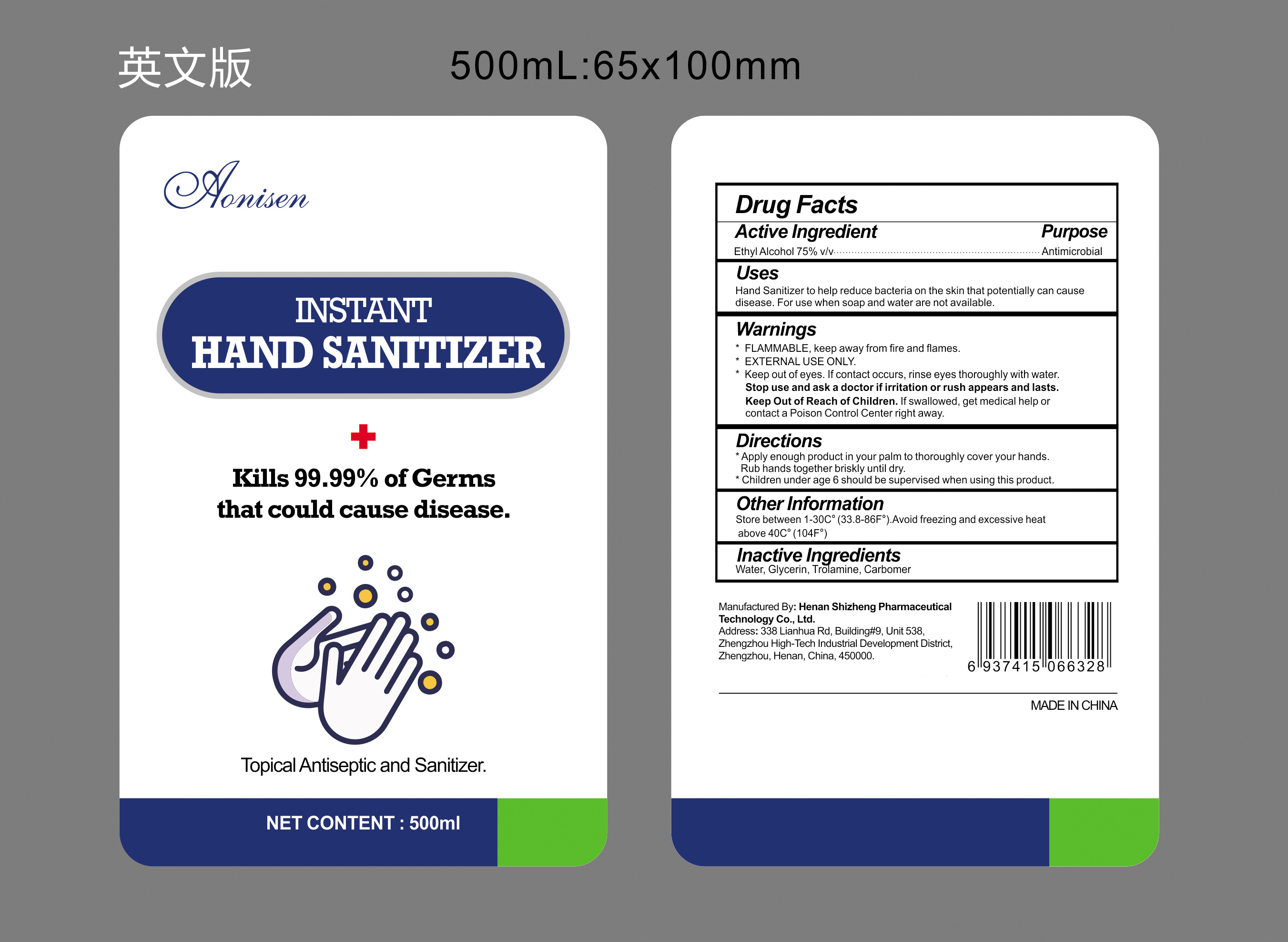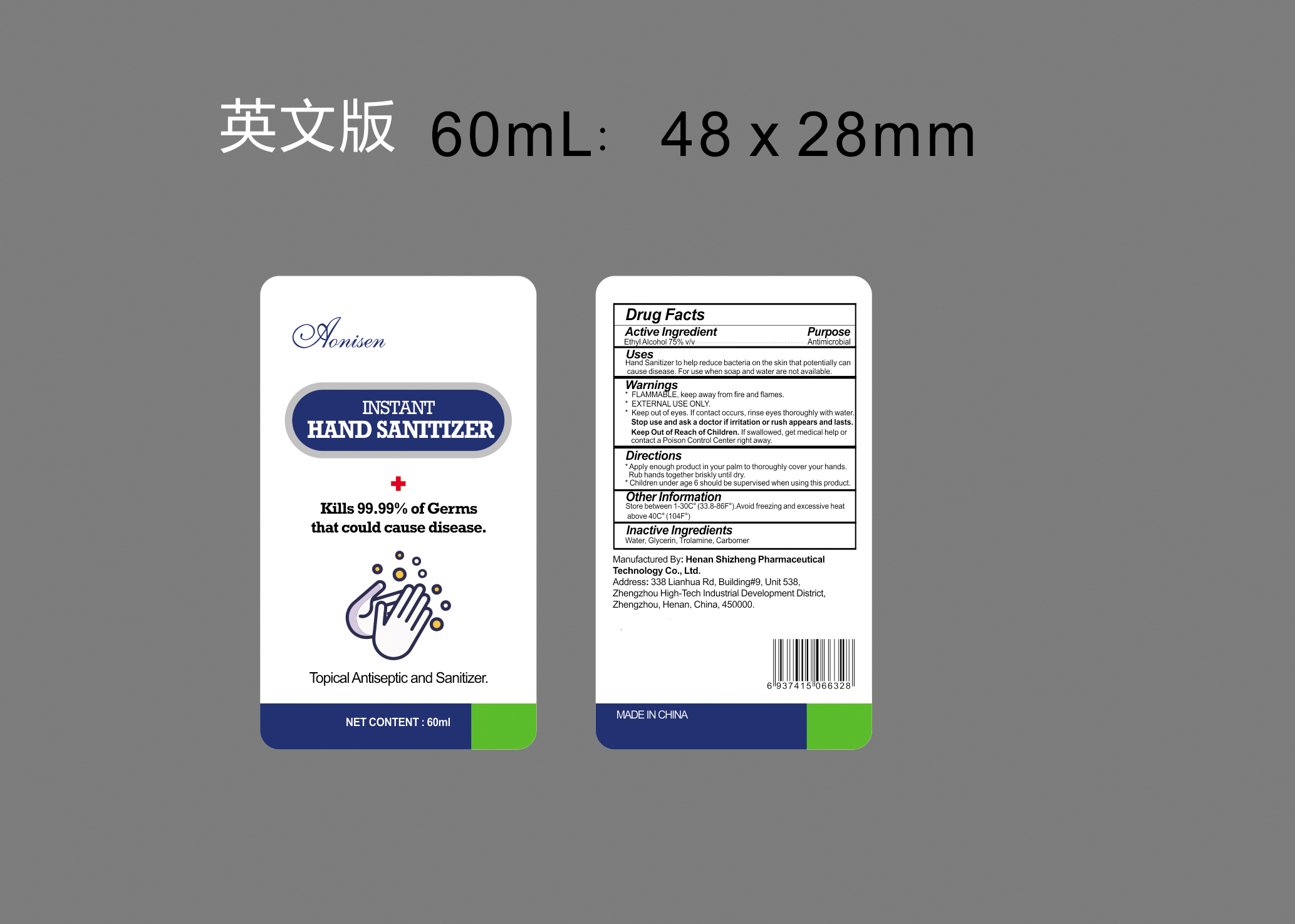 DRUG LABEL: Aonisen Hand Sanitizer
NDC: 75138-130 | Form: GEL
Manufacturer: Henan Shizheng Pharmaceutical Technology Co., Ltd.
Category: otc | Type: HUMAN OTC DRUG LABEL
Date: 20200509

ACTIVE INGREDIENTS: ALCOHOL 75 mL/100 mL
INACTIVE INGREDIENTS: CARBOMER HOMOPOLYMER, UNSPECIFIED TYPE 0.8 mL/100 mL; GLYCERIN 3 mL/100 mL; TROLAMINE 0.2 mL/100 mL; WATER 21 mL/100 mL

Aonisen HAND SANITIZER

This is a hand sanitizer manufactured according to the Temporary Policy for Preparation of Certain Alcohol-Based Hand Sanitizer Products During the Public Health Emergency (CoViD-19); Guidance for Industry.

The hand sanitizer is manufactured using only the following United States Pharmacopoeia (USP) grade ingredients in the preparation of the product (percentage in final product formulation) consistent with World Health Organization (WHO) recommendations:

1. Isopropyl Alcohol (75%, v/v) in an aqueous solution denatured according to Alcohol and Tobacco Tax and Trade Bureau regulations in 27 CFR part 20.
2. Glycerin (3% v/v).
3. Carbomer (0.8% v/v).
4. Trolamine(0.2% v/v).
5. water.

The firm does not add other active or inactive ingredients. Different or additional ingredients may impact the quality and potency of the product.

Active Ingredient(s)

Ethyl Alcohol 75% v/v. Purpose: Antiseptic

Purpose

Antiseptic, Hand Sanitizer

Use

Hand Sanitizer to help reduce bacteria on the skin that potentially can cause disease. For use when soap and water are not available.

WARNINGS

FLAMMABLE. Keep away from fire and flames.

EXTERNAL USE ONLY.

Keep out of eyes. If contact occurs, rinse eyes thoroughly with water.

Stop use and ask a doctor if irritation or rash occurs and lasts.

Keep out of reach of children. If swallowed, get medical help or contact a Poison Control Center right away.

Directions

Apply enough product in your palm to thoroughly cover your hands. Rub hands together briskly until dry.

Children under age 6 should be supervised when using this product.

Other information

- Store between 15-30C (59-86F)
- Avoid freezing and excessive heat above 40C (104F)

Inactive ingredients

Water,Glycerin, Trolamine, Carbomer

Package Label - Principal Display Panel

60 ml NDC: 75138-130-06 100 mL NDC: 75138-130-10

300 mL NDC: 75138-130-30

500 mL NDC: 75138-130-51 500 mL NDC: 75138-130-52

30 ml NDC: 75138-130-13